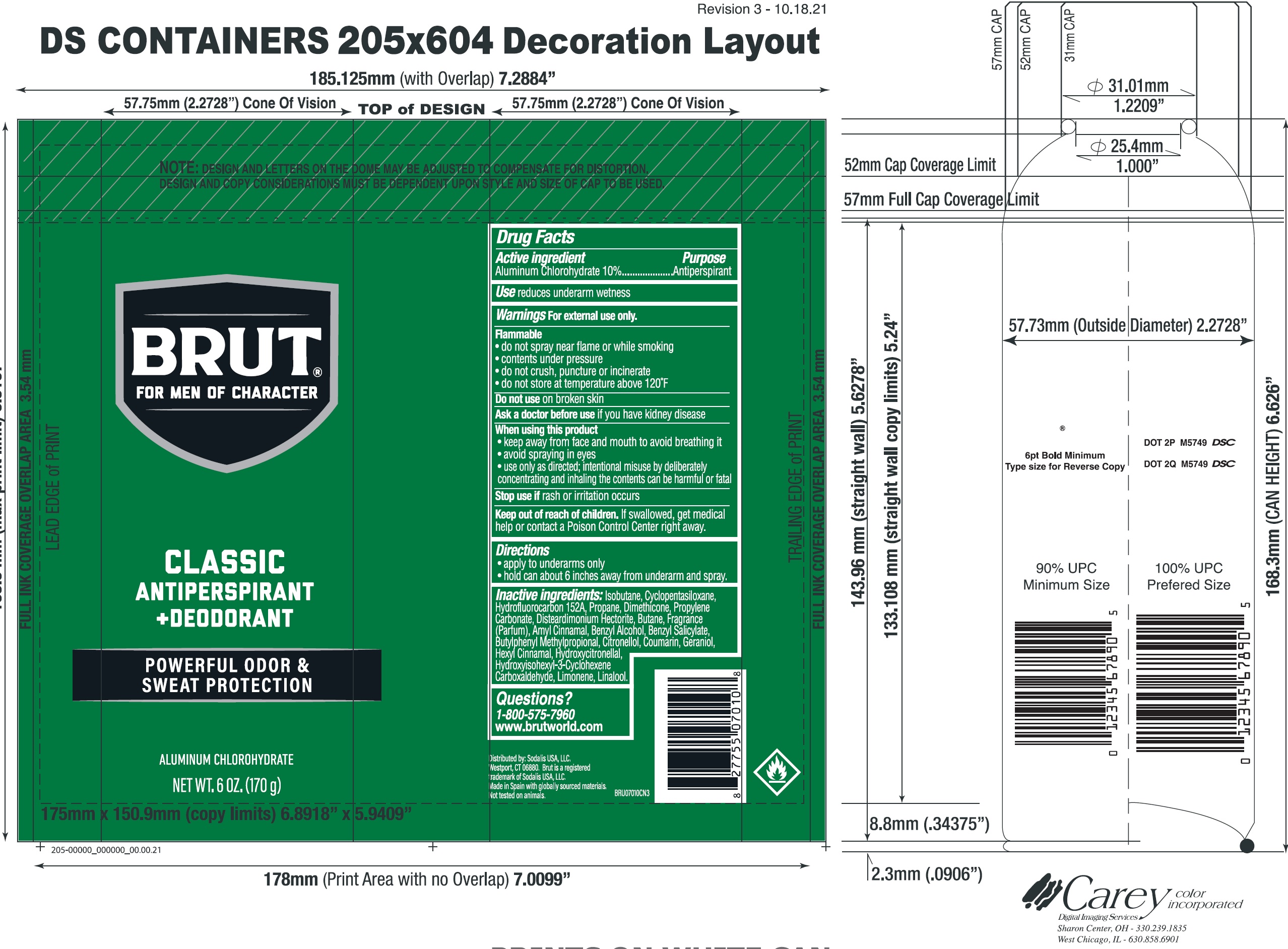 DRUG LABEL: Brut Classic Antiperspirant and Deodorant
NDC: 81277-012 | Form: AEROSOL, SPRAY
Manufacturer: Sodalis USA, LLC
Category: otc | Type: HUMAN OTC DRUG LABEL
Date: 20250218

ACTIVE INGREDIENTS: ALUMINUM CHLOROHYDRATE 100 mg/1 g
INACTIVE INGREDIENTS: ISOBUTANE; CYCLOPENTASILOXANE; HYDROFLUOROCARBON 152A; PROPANE; DIMETHICONE; PROPYLENE CARBONATE; DISTEARDIMONIUM HECTORITE; BUTANE; AMYL CINNAMAL; BENZYL ALCOHOL; BENZYL SALICYLATE; BUTYLPHENYL METHYLPROPIONAL; CITRONELLOL; COUMARIN; GERANIOL; HEXYL CINNAMAL; HYDROXYCITRONELLAL; HYDROXYISOHEXYL 3-CYCLOHEXENE CARBOXALDEHYDE; LIMONENE, (+)-; LINALOOL

Brut Classic Aerosol Antiperspirant and Deodorant

Active ingredient

Aluminum Chlorohydrate 10%

Purpose

Antiperspirant

Use

reduces underarm wetness

Warnings

For external use only.

Flammable

- do not spray near flame or while smoking
- contents under pressure
- do not crush, puncture or incinerate
- do not store at temperature above 120°F

Do not use

on broken skin

Ask a doctor before use

if you have kidney disease

When using this product

- keep away from face and mouth to avoid breathing it
- avoid spraying in eyes
- use only as directed; intentional misuse by deliberately concentrating and inhaling the contents can be harmful or fatal

Stop use if

rash or irritation occurs

Keep out of reach of children.

If swallowed, get medical help or contact a Poison Control Center right away.

Directions

- apply to underarms only
- hold can about 6 inches away from underarm and spray.

Inactive ingredients:

Isobutane, Cyclopentasiloxane, Hydrofluorocarbon 152A, Propane, Dimethicone, Propylene Carbonate, Disteardimonium Hectorite, Butane, Fragrance (Parfum), Amyl Cinnamal, Benzyl Alcohol, Benzyl Salicylate, Butylphenyl Methylpropional, Citronellol, Coumarin, Geraniol, Hexyl Cinnamal, Hydroxycitronellal, Hydroxyisohexyl-3-Cyclohexene Carboxaldehyde, Limonene, Linalool.

Questions?

1-800-575-7960

www.brutworld.com